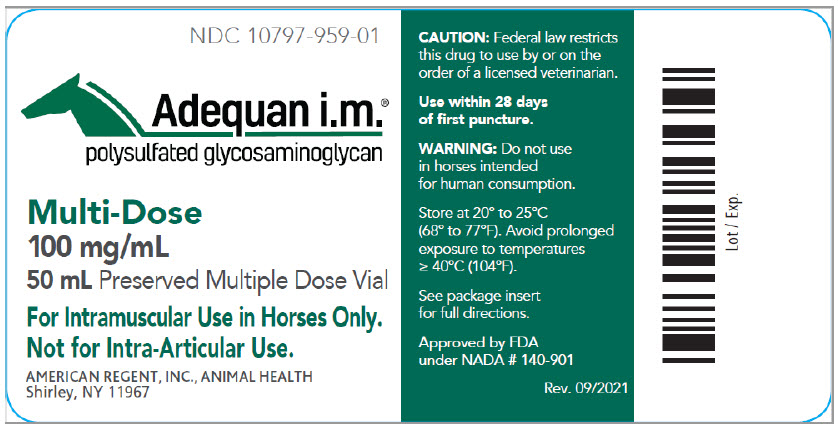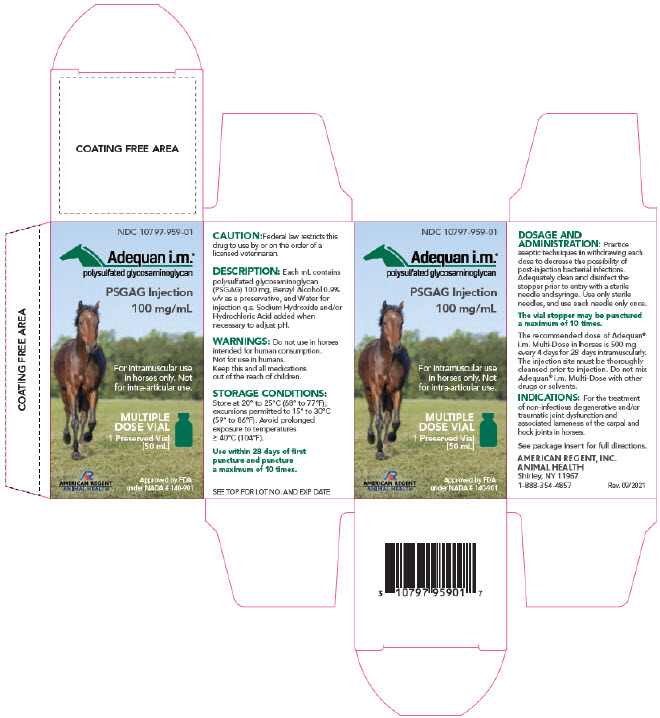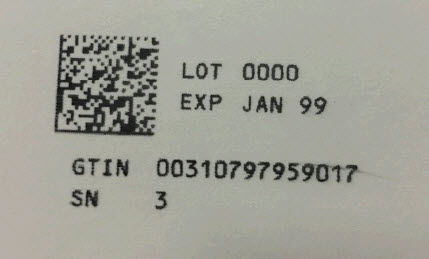 DRUG LABEL: Adequan i.m.
NDC: 10797-959 | Form: INJECTION, SOLUTION
Manufacturer: American Regent, Inc.
Category: animal | Type: PRESCRIPTION ANIMAL DRUG LABEL
Date: 20241007

ACTIVE INGREDIENTS: POLYSULFATED GLYCOSAMINOGLYCAN 100 mg/1 mL
INACTIVE INGREDIENTS: BENZYL ALCOHOL; WATER

Adequan i.m.®
polysulfated glycosaminoglycan

MULTI-DOSE
Solution 100 mg/mL in a 50 mL Preserved Multi-Dose Vial
For Intramuscular Use In Horses Only. Not for Intra-Articular Use.

CAUTION: Federal law restricts this drug to use by or on the order of a licensed veterinarian.

DESCRIPTION:

Each mL contains Polysulfated Glycosaminoglycan (PSGAG) 100 mg, Benzyl Alcohol 0.9% v/v as a preservative, and Water for Injection q.s. Sodium Hydroxide and/or Hydrochloric Acid added when necessary to adjust pH. The solution is clear, colorless to slightly yellow.

PHARMACOLOGY:

Polysulfated Glycosaminoglycan is chemically similar to the glycosaminoglycans in articular cartilage matrix. PSGAG is a potent proteolytic enzyme inhibitor and diminishes or reverses the pathologic processes of traumatic or degenerative joint disease which result in a net loss of cartilage matrix components. PSGAG improves joint function by reducing synovial fluid protein levels and increasing synovial fluid hyaluronic acid concentration in traumatized equine carpal and hock joints.

INDICATIONS:

Adequan® i.m. Multi-Dose is recommended for the intramuscular treatment of non-infectious degenerative and/or traumatic joint dysfunction and associated lameness of the carpal and hock joints in horses.

DOSAGE AND ADMINISTRATION:

Practice aseptic techniques in withdrawing each dose to decrease the possibility of post-injection bacterial infections. Adequately clean and disinfect the stopper prior to entry with a sterile needle and syringe. Use only sterile needles, and use each needle only once.

The vial stopper may be punctured a maximum of 10 times.

The recommended dose of Adequan® i.m. Multi-Dose in horses is 500 mg every 4 days for 28 days intramuscularly. The injection site must be thoroughly cleansed prior to injection. Do not mix Adequan® i.m. Multi-Dose with other drugs or solvents.

CONTRAINDICATIONS:

There are no known contraindications to the use of intramuscular Polysulfated Glycosaminoglycan.

WARNINGS:

Do not use in horses intended for human consumption. Not for use in humans. Keep this and all medications out of the reach of children.

PRECAUTIONS:

The safe use of Adequan® i.m. Multi-Dose in horses used for breeding purposes, during pregnancy, or in lactating mares has not been evaluated.

Safety and efficacy studies utilizing Adequan® i.m. Multi-Dose were not performed. Adequan® i.m. Multi-Dose was approved based on the conclusion that the safety and effectiveness of Adequan® i.m. Multi-Dose will not differ from that demonstrated for the original formulation of Adequan® i.m.

ANIMAL SAFETY:

Animal Safety studies utilizing Adequan® i.m. Multi-Dose were not performed. Safety studies were conducted in horses using the single dose formulation. Doses as high as 2,500 mg were administered intramuscularly to 6 horses twice a week for 12 weeks. This dosage is 5 times the recommended dosage and 3 times the recommended therapeutic regimen. Clinical observations revealed no soreness or swelling at the injection site or in the affected joint. No animal had any clinical or laboratory evidence of toxicity.

STORAGE CONDITIONS:

Store at 20°-25°C (68°-77°F); excursions permitted to 15°-30°C (59°-86°F) (See USP Controlled Room Temperature). Avoid prolonged exposure to temperatures ≥ 40°C (104°F).

Use within 28 days of first puncture and puncture a maximum of 10 times. Dispose of spent needles in accordance with all federal, state and local environmental laws.

HOW SUPPLIED:

Adequan® i.m. Multi-Dose solution, 5,0000 mg/50 mL (100 mg/mL) in 50 mL multi-dose glass vials.
NDC 10797-959-01 50 mL Multi-Dose Vials Packaged 1 vial per box

AMERICAN REGENT, INC.
ANIMAL HEALTH
Shirley, NY 11967
(1-888-354-4857)

Made in U.S.A.
IN959
Rev. 9/2021
MG# 44453

Approved by FDA under NADA #140-901

Container Label

NDC 10797-959-01

Adequan i.m.®
polysulfated glycosaminoglycan

Multi-Dose

100 mg/mL
50 mL Preserved Multiple Dose Vial

For Intramuscular Use in Horses Only. Not for Intra-Articular Use.
CAUTION: Federal law restricts this drug to use by or on the order of a licensed veterinarian.

Use within 28 days of first puncture.

WARNING: Do not use in horses intended for human consumption.

Store at 20° to 25°C (68° to 77°F). Avoid prolonged exposure to temperatures ≥ 40°C (104°F).

See package insert for full directions.
AMERICAN REGENT, INC.
ANIMAL HEALTH
Shirley, NY 11967

Approved by the FDA under NADA # 140-901

Rev. 09/2021

Carton Labeling

NDC 10797-959-01

Adequani.m.®
polysulfated glycosaminoglycan
PSGAG Injection
100 mg/mL
For intramuscular use in horses only. Not for intra-articular use.

MULTIPLE DOSE VIAL

1 Preserved Vial
[50 mL]

AMERICAN REGENT, INC.
ANIMAL HEALTH

Approved by FDA under NADA # 140-901